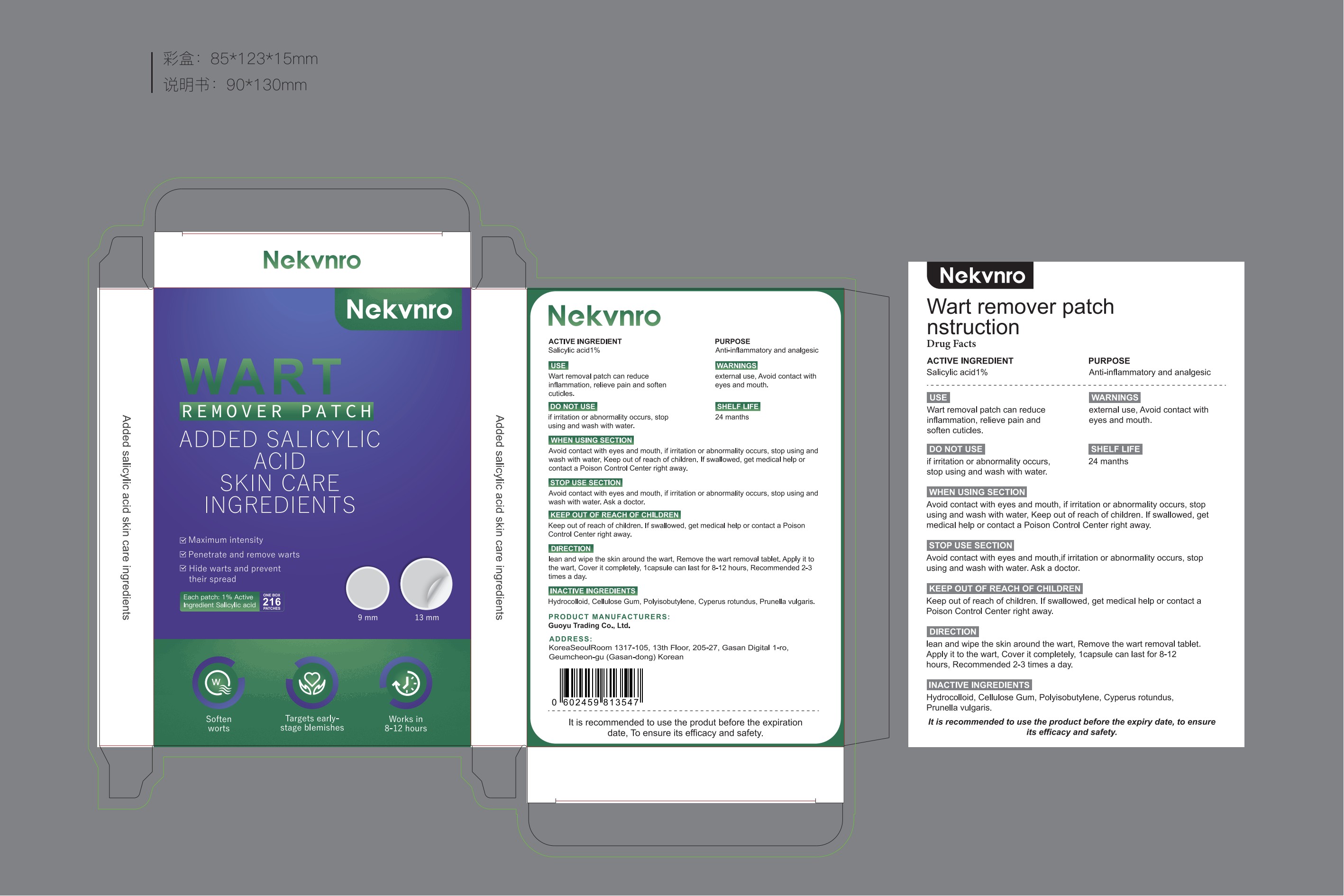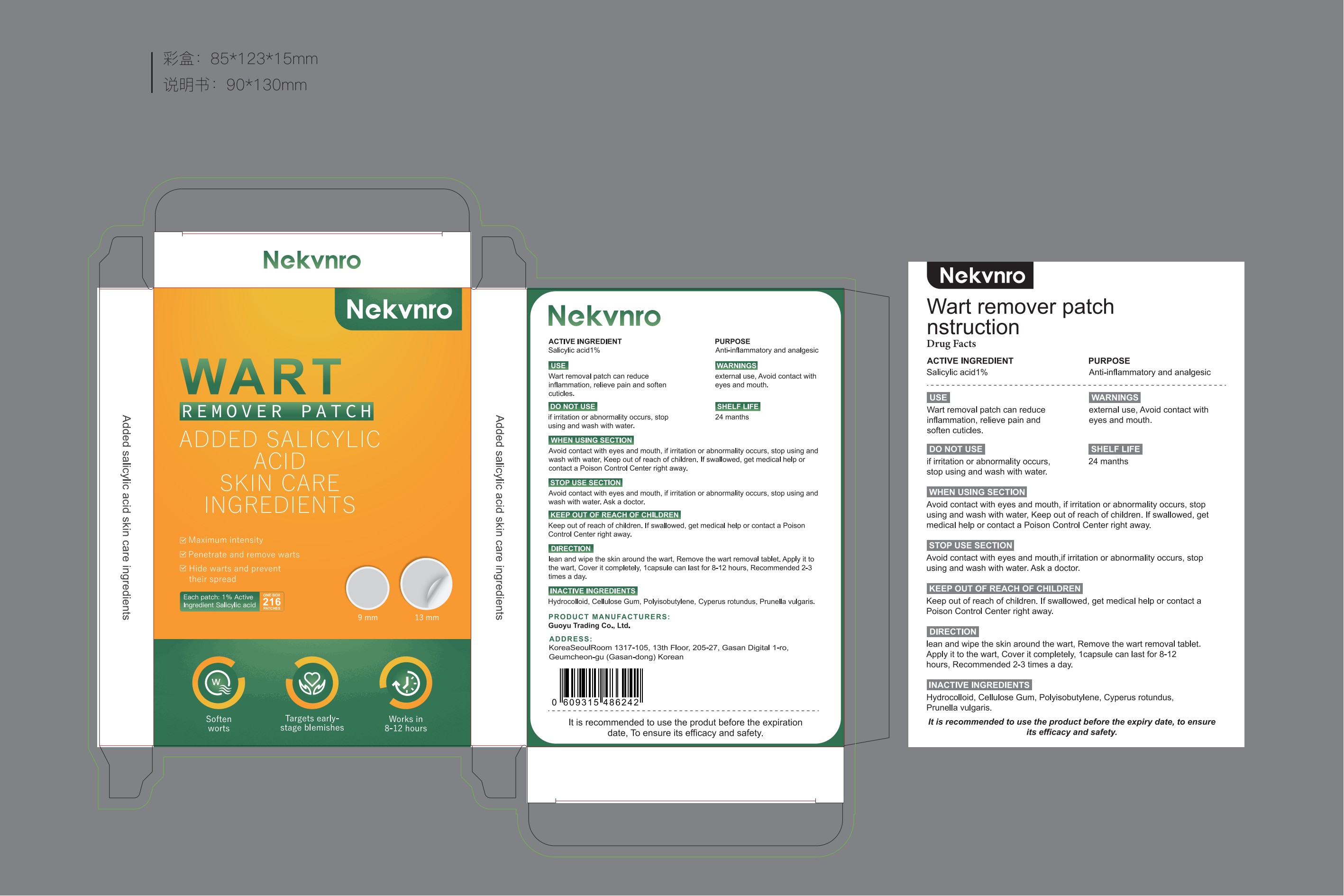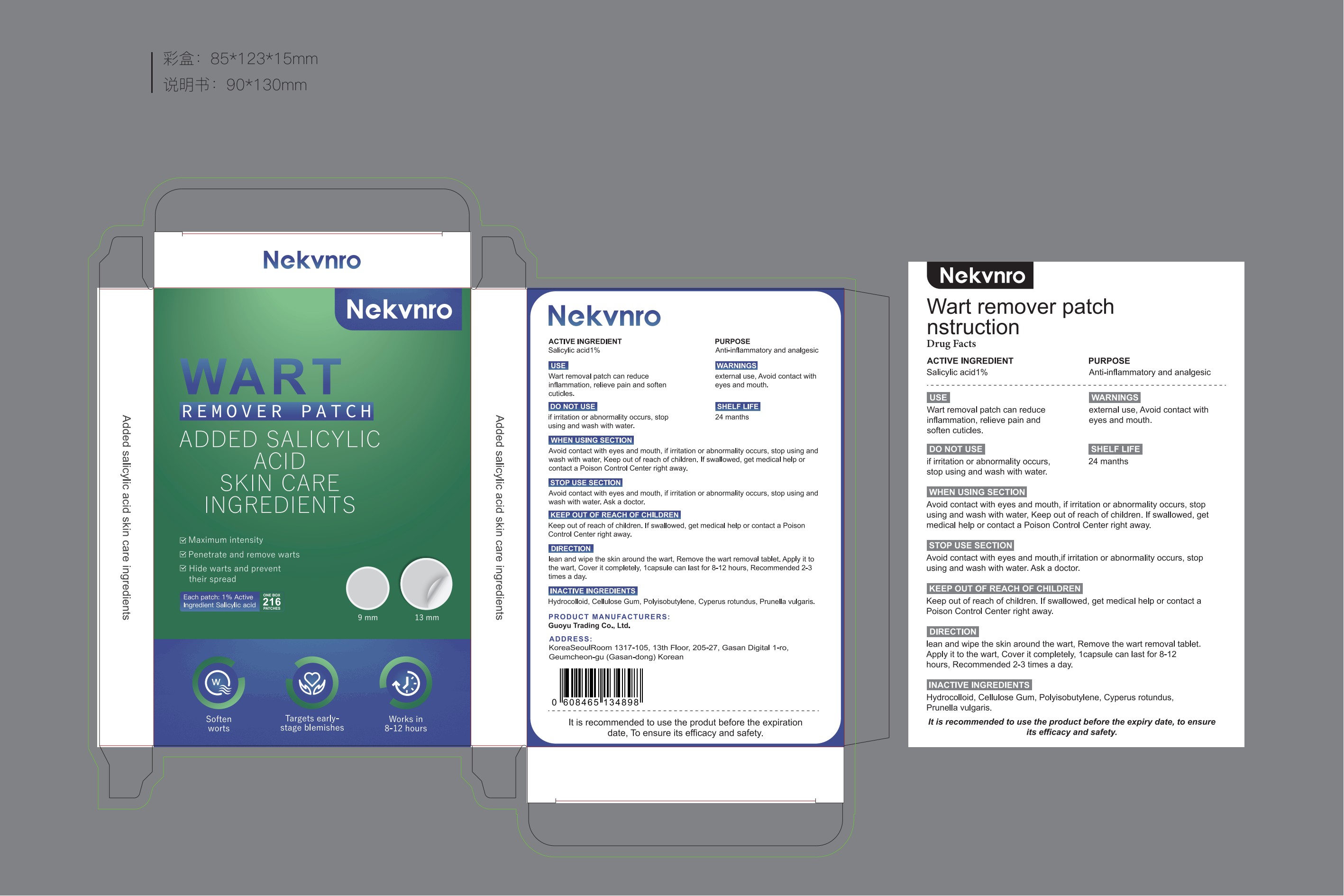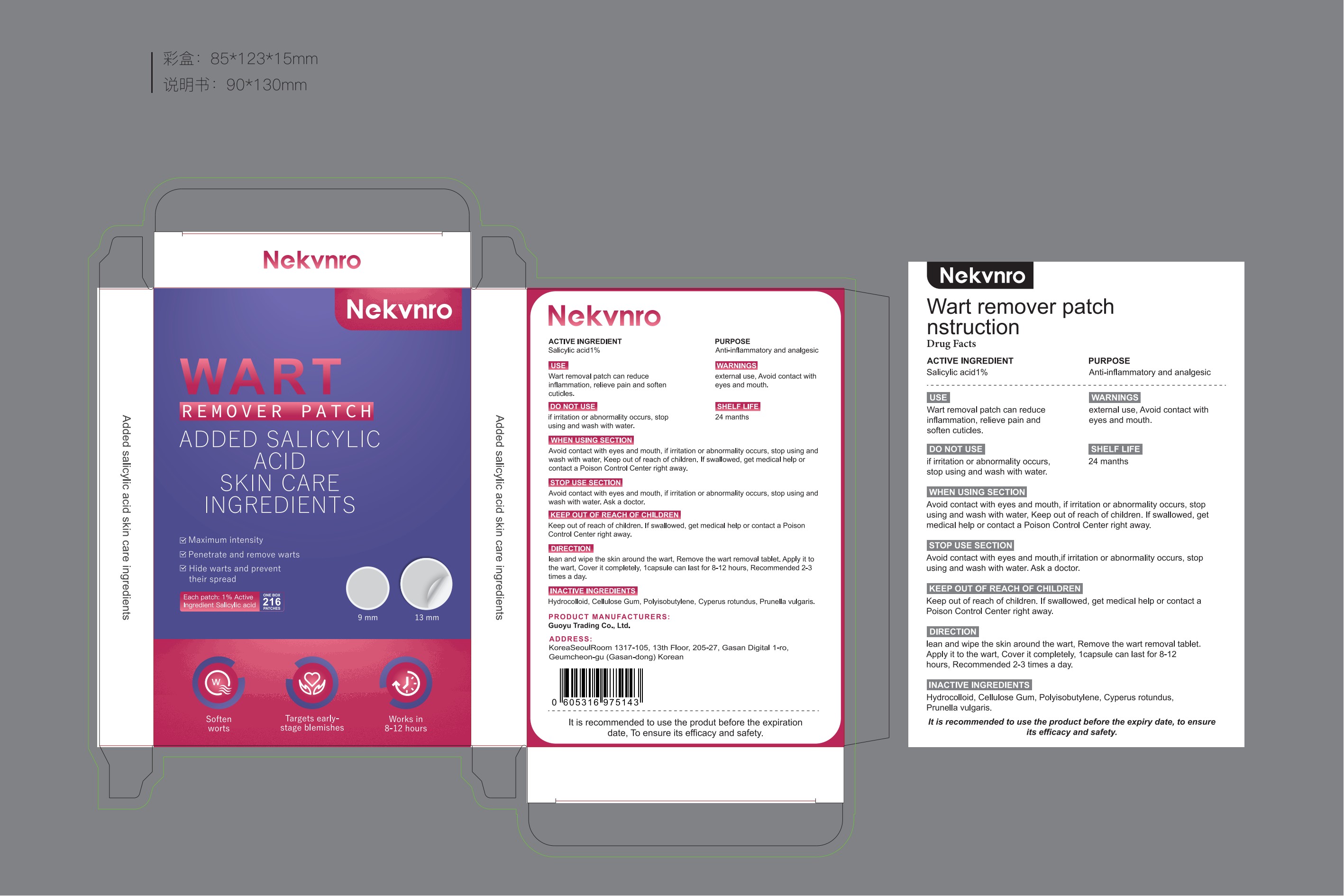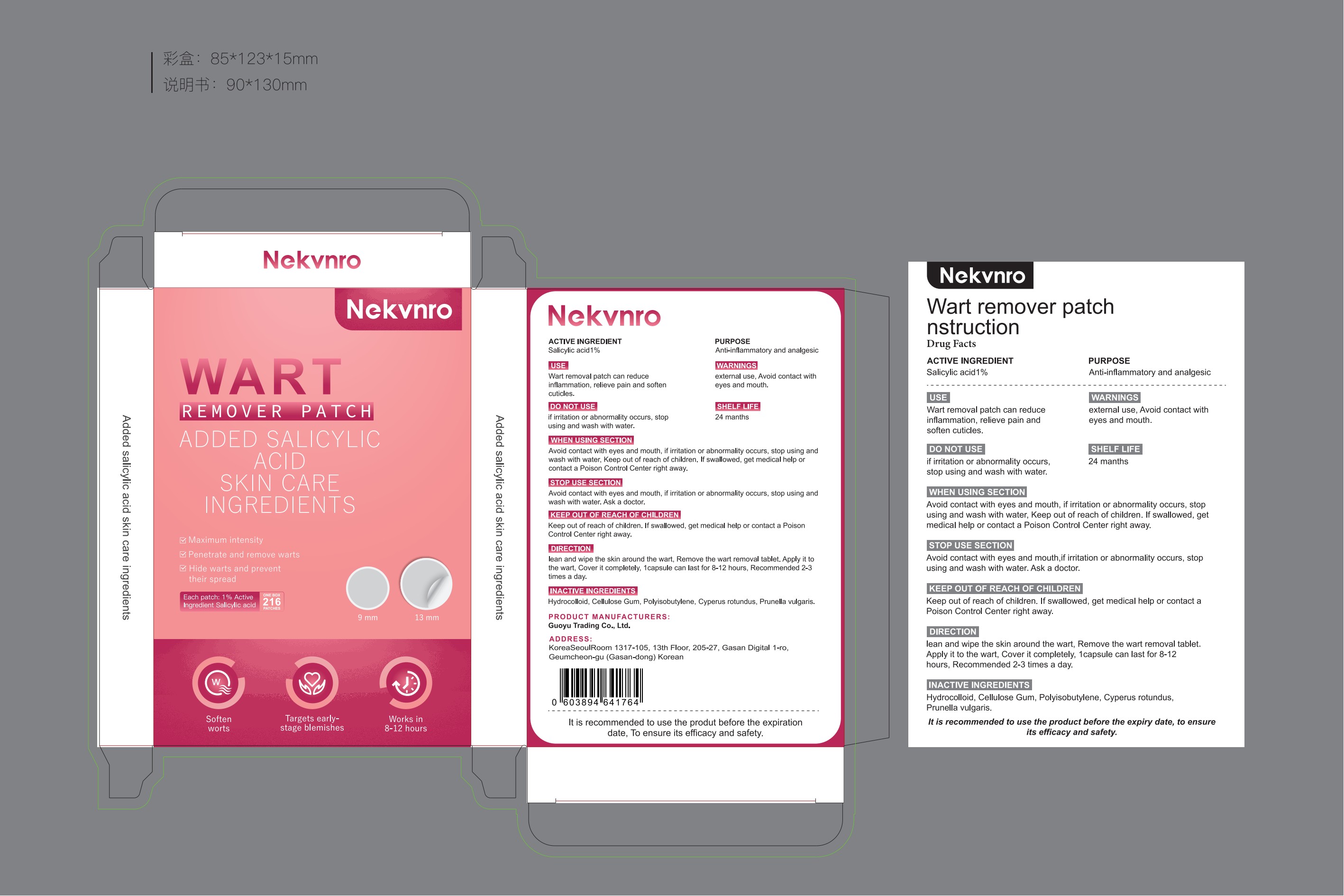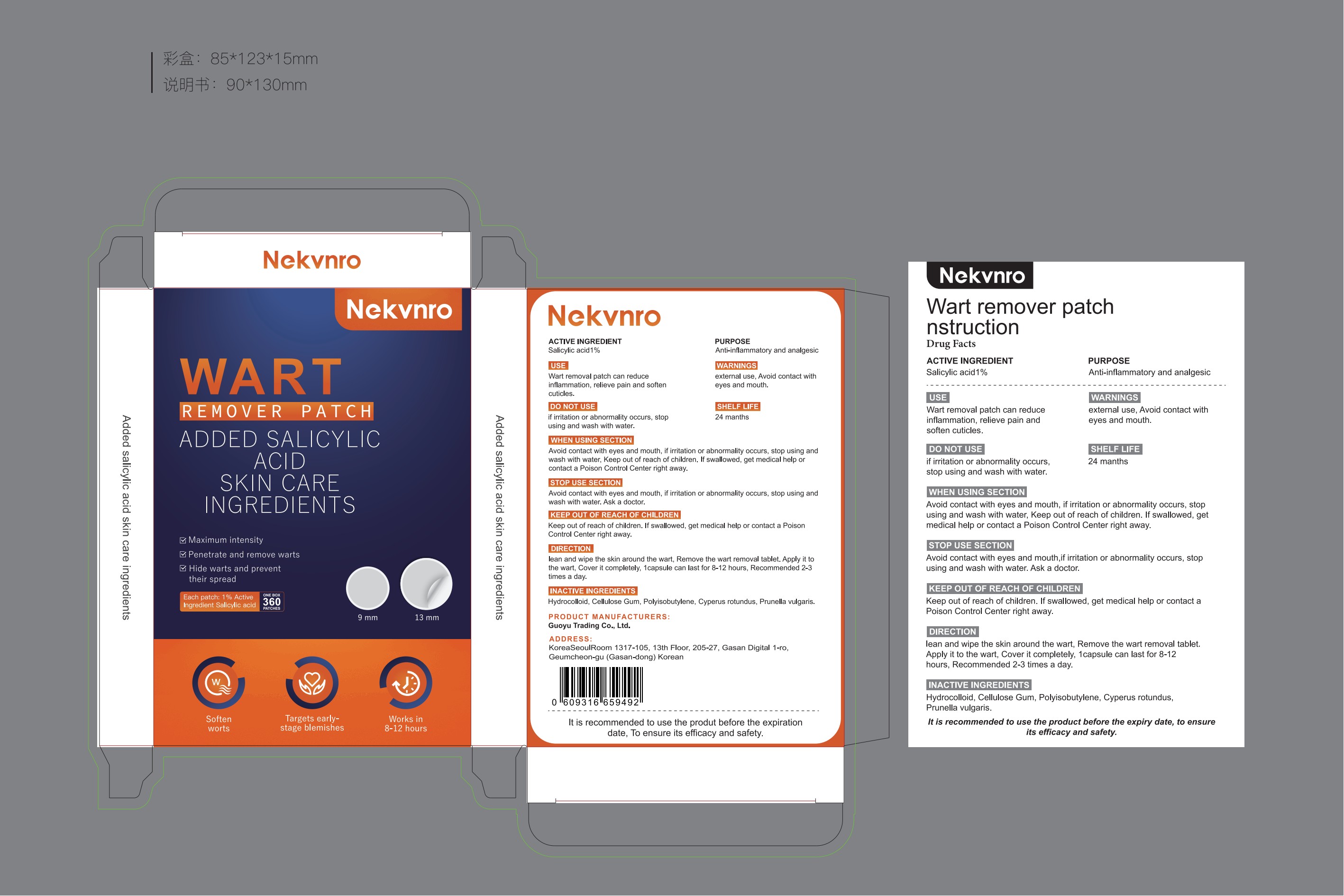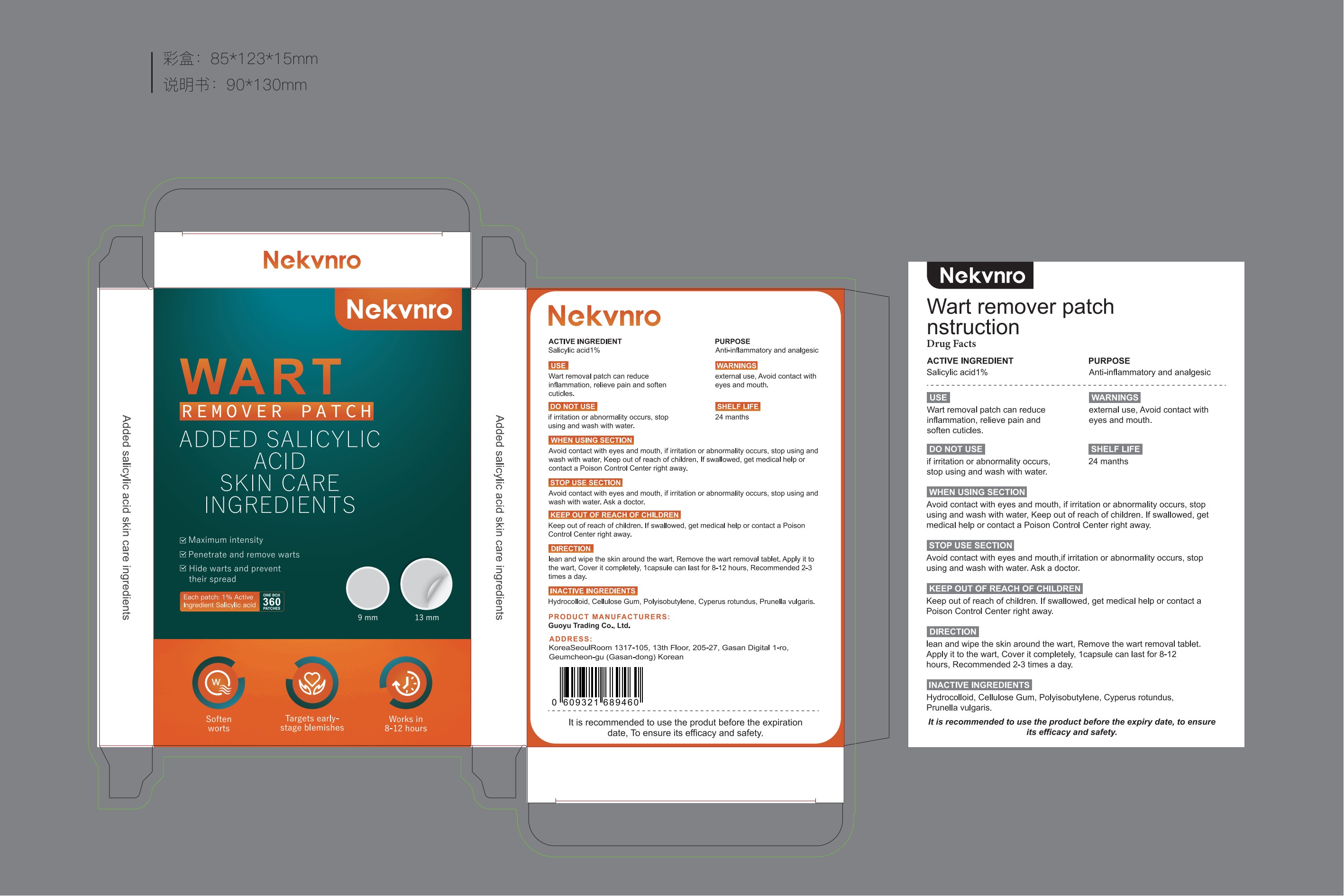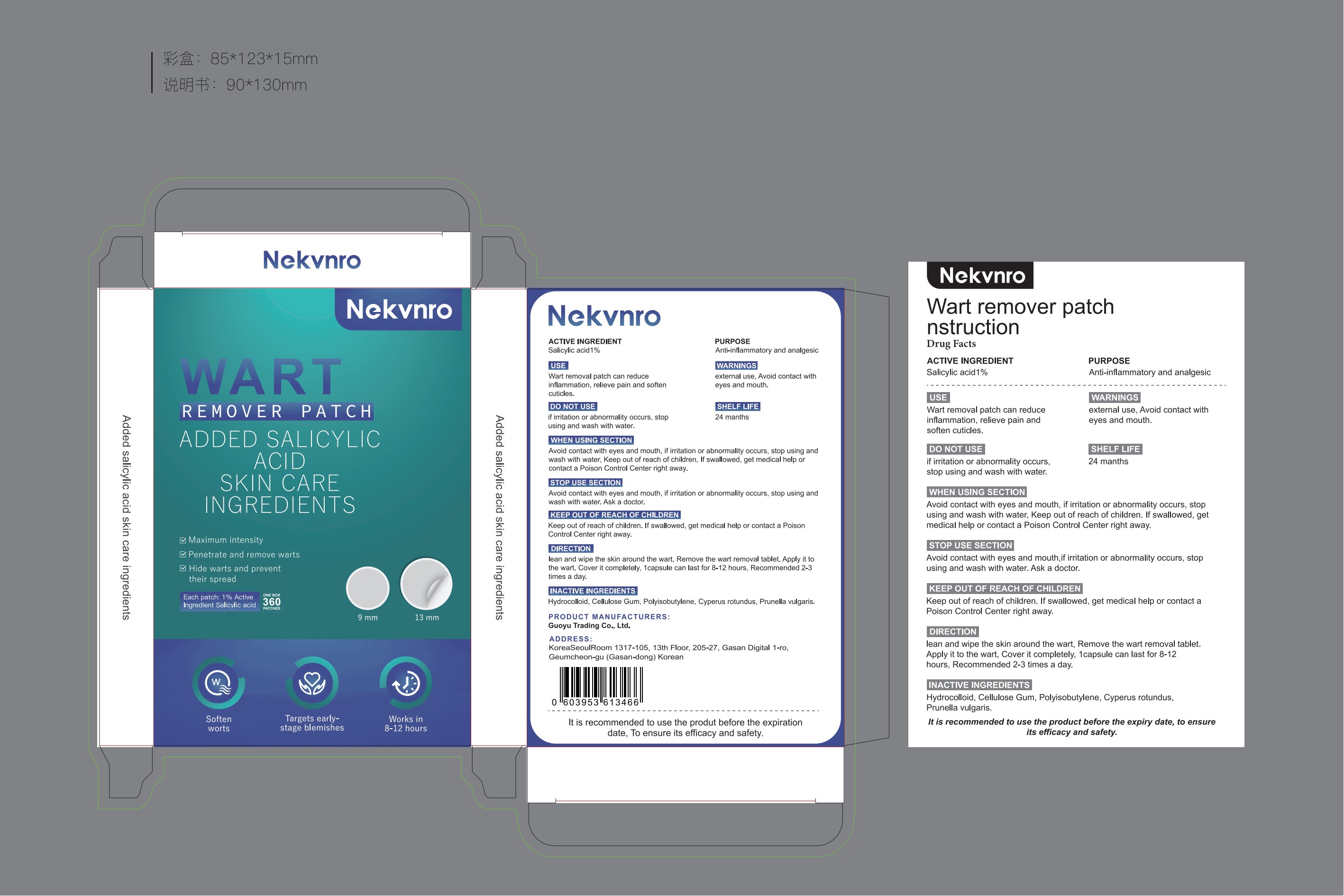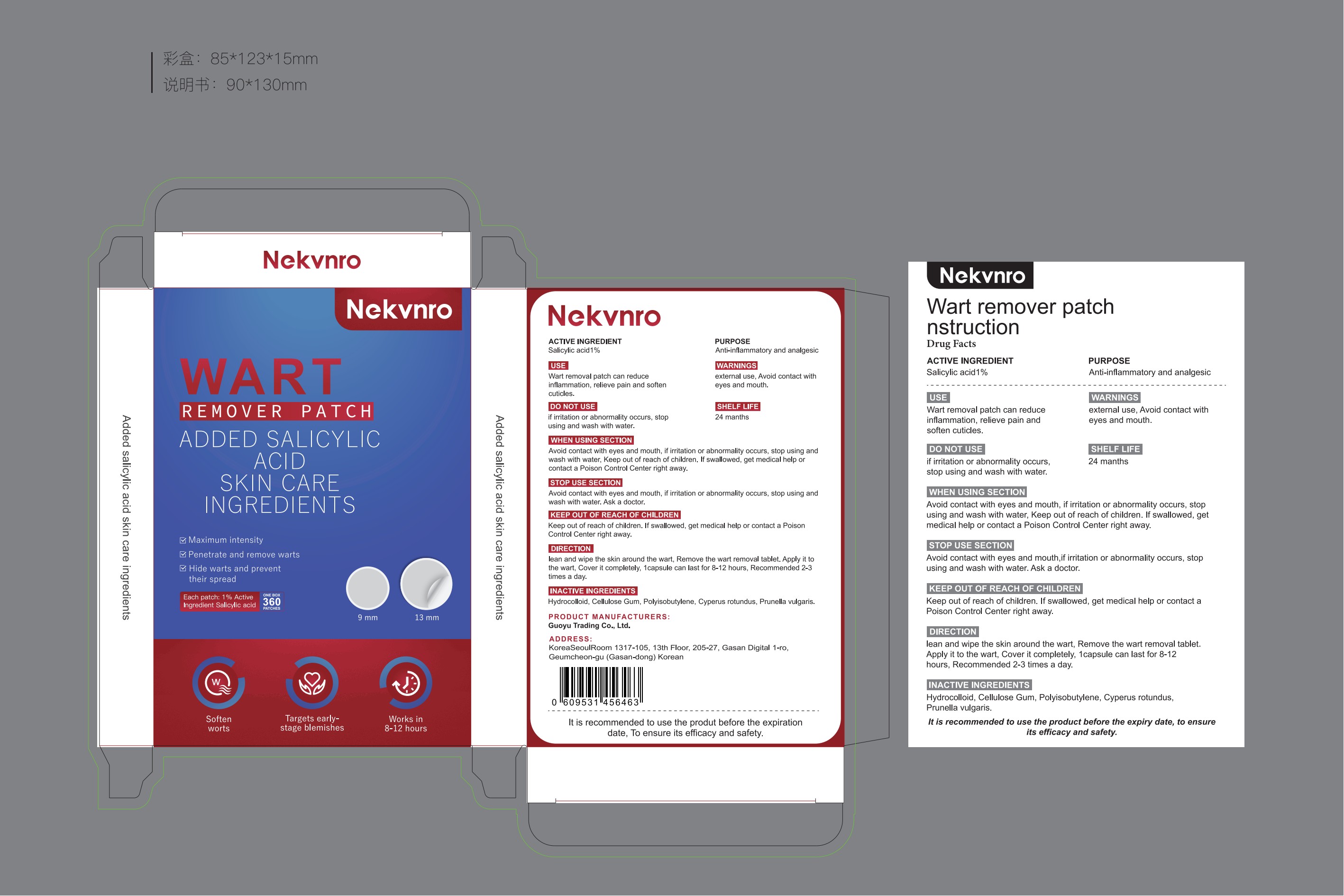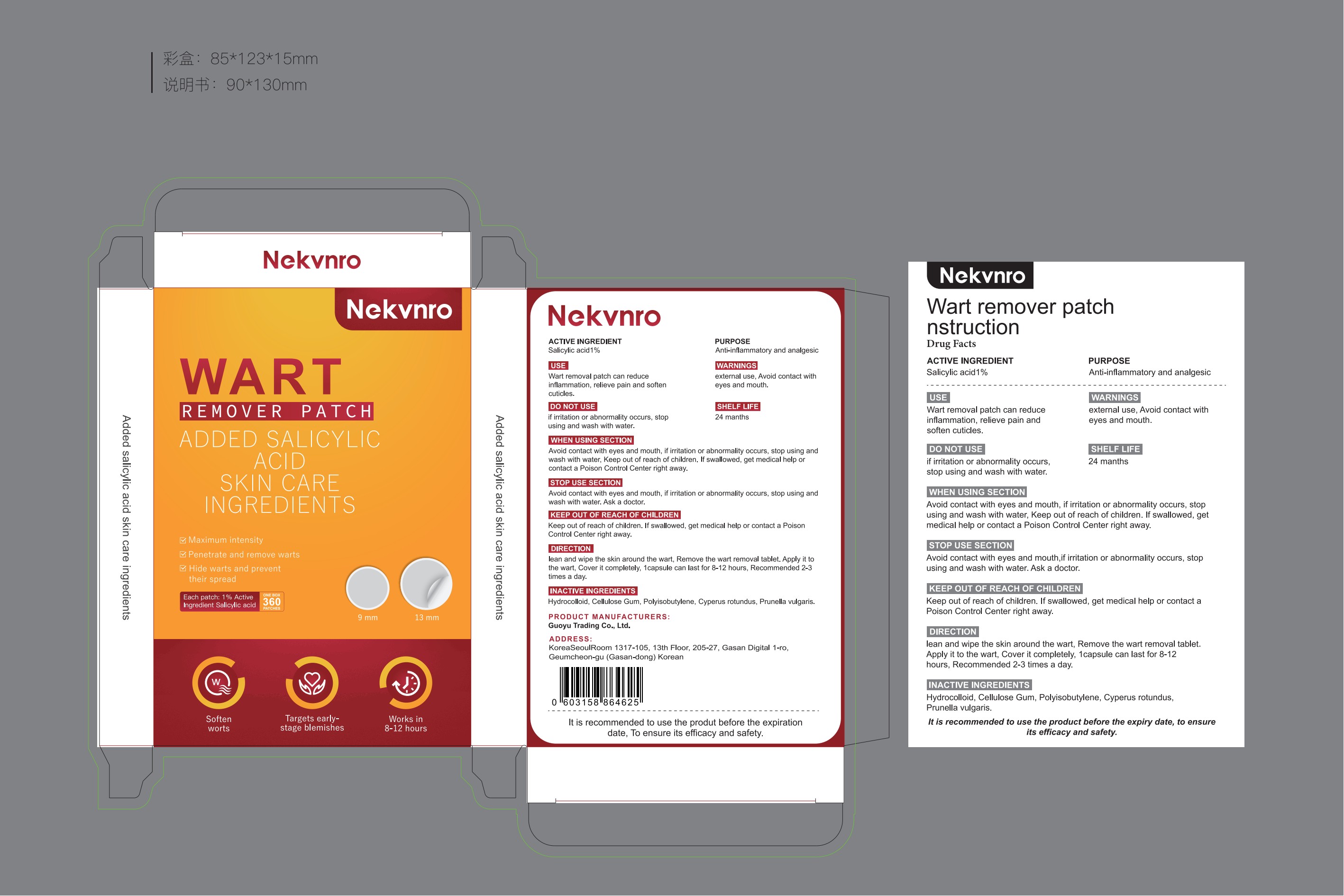 DRUG LABEL: Nekvnro Wart Remover Patch
NDC: 84844-002 | Form: PATCH
Manufacturer: Guoyu Trading Co., Ltd.
Category: otc | Type: HUMAN OTC DRUG LABEL
Date: 20241023

ACTIVE INGREDIENTS: SALICYLIC ACID 1 g/100 1
INACTIVE INGREDIENTS: CELLULOSE GUM; CYPERUS PROLIFER WHOLE; PRUNELLA VULGARIS; POLYISOBUTYLENE (1100000 MW); 1-DODECYLPERHYDROAZEPINE-1-OXIDE

84844-002

Active Ingredient

Salicylic acid 1%

Purpose

Anti-inflammatory and analgesic

Use

Wart removal patch can reduce inflammation, relieve pain and soften cuticles.

Warnings

external use,Avoid contact with eyes and mouth.

Do not use

if irritation or abnormality occurs, stop using and wash with water.

When Using

Avoid contact with eyes and mouth,if irritation or abnormality occurs, stop using and wash with water,Keep out of reach of children. If swallowed, get medical help or contact a Poison Control Center right away.

Stop Use

Avoid contact with eyes and mouth,if irritation or abnormality occurs, stop using and wash with water.

Ask Doctor

If swallowed, get medical help or contact a Poison Control Center right away.

Keep Oot Of Reach Of Children

If swallowed, get medical help or contact a Poison Control Center right away.

Directions

lean and wipe the skin around the wart，Remove the wart removal tablet.Apply it to the wart,Cover it completely，1capsule can last for 8-12 hours, Recommended 2-3 times a day.

Inactive ingredients

Hydrocolloid,Cellulose Gum,Polyisobutylene,Polyisobutylene，Cyperus rotundus，Prunella vulgaris.